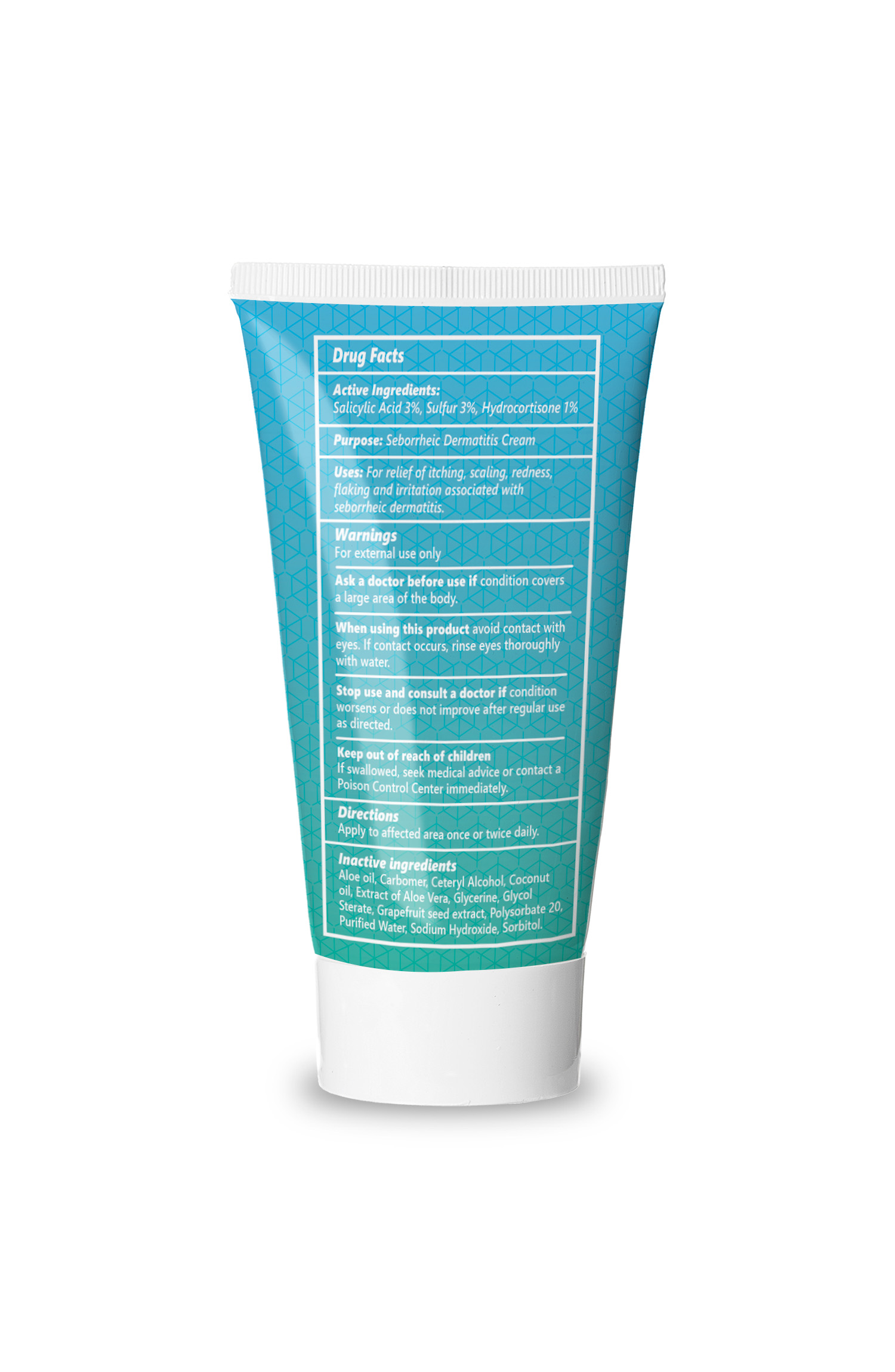 DRUG LABEL: DERMOSCRIBE SEBORRHEIC DERMATITIS
NDC: 69683-202 | Form: CREAM
Manufacturer: DERMOSCRIBE PTY LTD
Category: otc | Type: HUMAN OTC DRUG LABEL
Date: 20251017

ACTIVE INGREDIENTS: SULFUR 3 g/100 g; SALICYLIC ACID 3 g/100 g; HYDROCORTISONE 1 g/100 g
INACTIVE INGREDIENTS: ALOE; GRAPEFRUIT; ALOE VERA LEAF OIL; CETOSTEARYL ALCOHOL; CARBOMER HOMOPOLYMER TYPE C; GLYCOL STEARATE SE; SORBITOL; GLYCERIN; COCONUT OIL; POLYSORBATE 20; SODIUM HYDROXIDE; WATER

DERMOSCRIBE (as PLD) - SEBORRHEIC DERMATITIS CREAM (69683-202)

ACTIVE INGREDIENTS

Sulfur 3%, Salicylic Acid 3%, Hydrocortisone 1%

PURPOSE

SEBORRHEIC DERMATITIS CREAM

USE

For relief of itching, scaling, redness, flaking and irritation associated with seborrheic dermatitis

WARNINGS

FOR EXTERNAL USE ONLY.

Ask a doctor before use if condition covers a large area of the body

When using this product avoid contact with eyes. If contact occurs, rinse eye thoroughly with water

Stop use and consult a doctor if condition worsens or does not improve after regular use as directed

KEEP OUT OF REACH OF CHILDREN. If swallowed, seek medical advice or contact a Poison Control Center immediately

DIRECTIONS

Apply to affected area once or twice daily

INACTIVE INGREDIENTS

Aloe Oil, Carbomer, Ceteryl Alcohol, Coconut Oil, Extract of Aloe Vera, Glycerine, Glycol Sterate, Grapefruit Seed Extract, Polysorbate 20, Purified Water, Sodium Hydroxide, Sorbitol

RECENT MAJOR CHANGES

Update drug facts